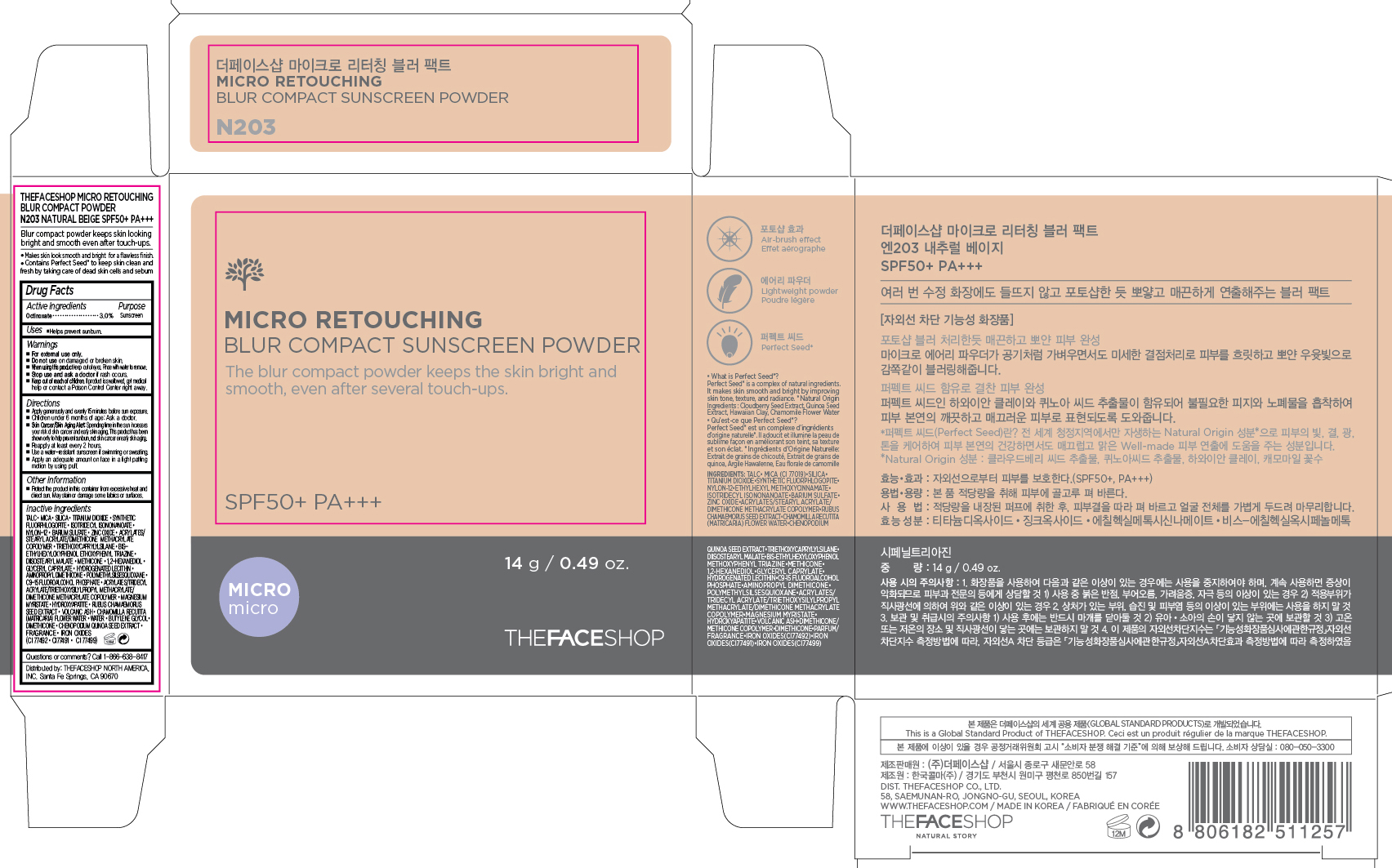 DRUG LABEL: MICRO RETOUCHING
NDC: 51523-377 | Form: POWDER
Manufacturer: THEFACESHOP CO., LTD.
Category: otc | Type: HUMAN OTC DRUG LABEL
Date: 20150928

ACTIVE INGREDIENTS: OCTINOXATE 0.42 g/14 g
INACTIVE INGREDIENTS: WATER

MICRO RETOUCHING BLUR COMPACT SUNSCREEN POWDER N203 NATURAL BEIGE SPF 50+ PA+++ 34200377

Active Ingredient

Octinoxate 3.0 %

Purpose

Sunscreen

Uses:

Helps prevent sunburn.

Warnings:

For external use only.

Do not use on damaged or broken skin

When using this product keep out of eyes. Rinse with water to remove.

Stop use and ask a doctor if rash occurs.

Keep out of reach of children. If product is swallowed, get medical help or contact a Poison Control Center right away.

Directions

Apply generously and evenly 15 minutes before sun exposure.
Children under 6 months of age: Ask a doctor.
Skin Cancer/Skin Aging Alert: Spending time in the sun increases your risk of skin cancer and early skin aging. This product has been shown only to help prevent sunburn, not skin cancer or early skin aging.
Reapply at least every 2 hours.
Use a water-resistant sunscreen if swimming or sweating.

Apply an adequate amount on face in a light patting motion by using puff.

OTHER SAFETY INFORMATION

Protect the product in this container from excessive heat and direct sun.

May stain or damage some fabrics or surfaces.

Inactive Ingredients:

TALC, MICA, SILICA, TITANIUM DIOXIDE, SYNTHETIC FLUORPHLOGOPITE, ISOTRIDECYL ISONONANOATE, NYLON-12, BARIUM SULFATE, ZINC OXIDE, ACRYLATES/STEARYL ACRYLATE/DIMETHICONE METHACRYLATE COPOLYMER, TRIETHOXYCAPRYLYLSILANE, BIS-ETHYLHEXYLOXYPHENOL ETHOXYPHENYL TRIAZINE, DIISOSTEARYL MALATE, METHICONE, 1,2-HEXANEDIOL, GLYCERYL CAPRYLATE, HYDROGENATED LECITHIN, AMINOPROPYL DIMETHICONE, POLYMETHYLSILSESQUIOXANE, C9-15 FLUOROALCOHOL PHOSPHATE, ACRYLATES/TRIDECYL ACRYLATE/TRIETHOXYSILYLPROPYL METHACRYLATE/DIMETHICONE METHACRYLATE COPOLYMER, MAGNESIUM MYRISTATE, HYDROXYAPATITE, RUBUS CHAMAEMORUS SEED EXTRACT, VOLCANIC ASH, CHAMOMILLA RECUTITA (MATRICARIA) FLOWER WATER, WATER, BUTYLENE GLYCOL, DIMETHICONE, CHENOPODIUM QUINOA SEED EXTRACT, FRAGRANCE, IRON OXIDES(CI 77492, CI77491 and CI 77499)

Questions or comments? Call 1-866-638-8417

Distributed by:

THEFACESHOP NORTH AMERICA, INC.

Santa Fe Springs, CA 90670

PACKAGE LABEL

MICRO RETOUCHING

BLUR COMPACT SUNSCREEN POWDER

V203 NATURAL BEIGE SPF50+ PA+++

Blur compact powder keeps skin looking bright and smooth even after touch-ups.

Makes skin look smooth and bright for a flawless finish.

Contains Perfect Seed to keep skin clean and fresh by taking care of dead cells and sebum.